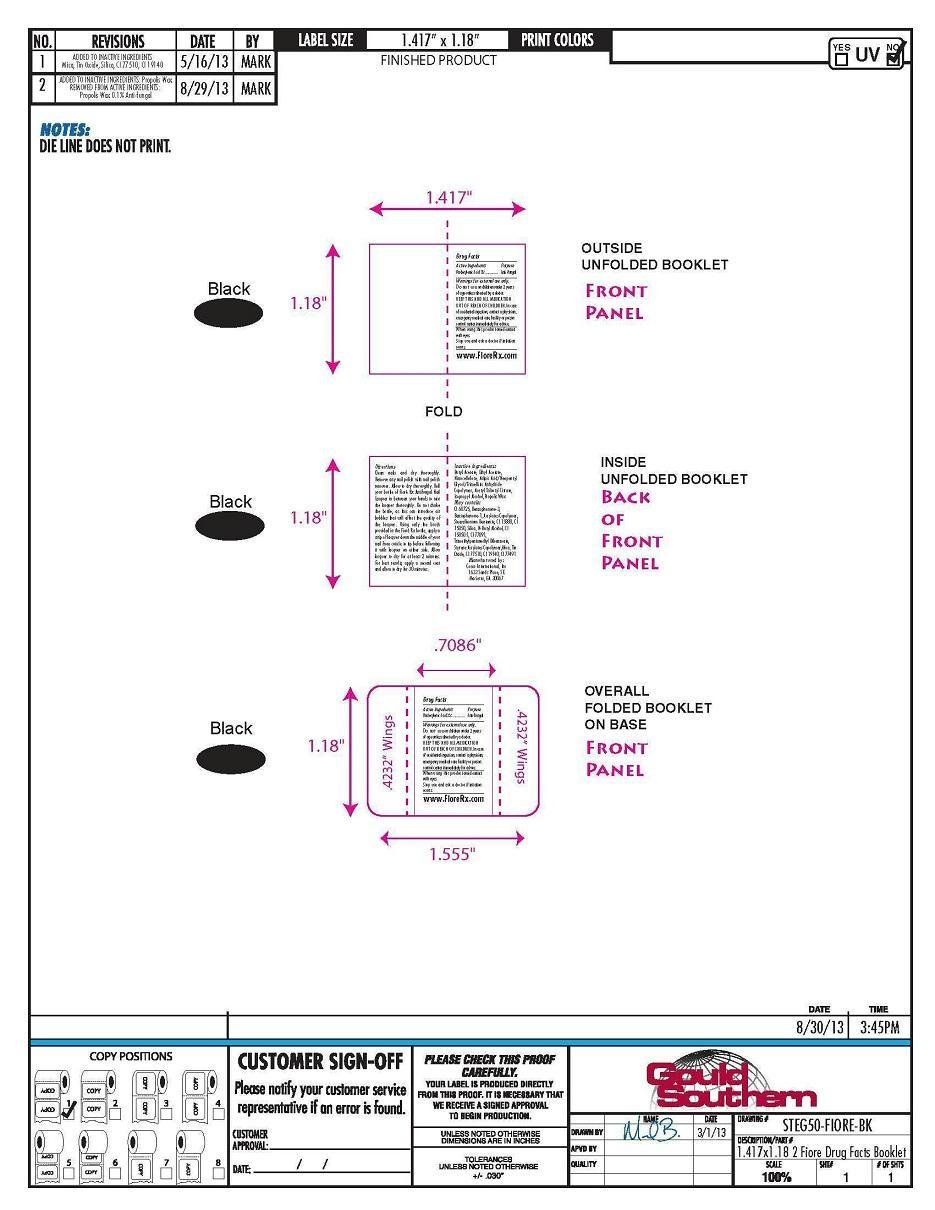 DRUG LABEL: Fiore Rx Pink Peppermint Pie Antifungal Nail Polish
NDC: 52261-0200 | Form: FILM
Manufacturer: Cosco International, Inc.
Category: otc | Type: HUMAN OTC DRUG LABEL
Date: 20130919

ACTIVE INGREDIENTS: Undecylenic Acid 0.45 g/15 mL
INACTIVE INGREDIENTS: Butyl Acetate 5.483175 g/15 mL; Ethyl Acetate 3.353295 g/15 mL; Pyroxylin 2.081865 g/15 mL; POLYESTER-10 1.059525 g/15 mL; Acetyltributyl Citrate 1.040925 g/15 mL; Isopropyl Alcohol 0.89223 mL/15 mL; BENTOQUATAM 0.17844 g/15 mL; DIMETHYLAMINOETHYL METHACRYLATE - BUTYL METHACRYLATE - METHYL METHACRYLATE COPOLYMER 0.167295 g/15 mL; TITANIUM DIOXIDE 0.0939 g/15 mL; Polacrilin 0.074355 g/15 mL; D&C RED NO. 6 0.03564 g/15 mL; Silicon Dioxide 0.029745 g/15 mL; Benzoresorcinol 0.029745 g/15 mL; PROPOLIS WAX 0.015 g/15 mL; Trimethylpentanediyl Dibenzoate 0.014865 g/15 mL

Drug Facts

Active Ingredient Purpose
Undecylenic Acid 3%........................Anti-fungal

PURPOSE

Anti-fungal

Warnings For external use only.

Do not use on children under 2 years of age unless directed by a doctor.

KEEP THIS AND ALL MEDICATION OUT OF REACH OF CHILDREN.

In case of accidental ingestion, contact a physician, emergency medical care facility or poison control center immediately for advice.

When using this product avoid contact with eyes.

Stop use and ask a doctor if irritation occurs.

Directions

Clean nails and dry thoroughly.

Remove any nail polish with nail

polish remover. Allow to dry

thoroughly. Roll your bottle of Fioré

Rx Antifungal Nail Lacquer in between

your hands to mix the lacquer

thoroughly. Do not shake the bottle,

as this can introduce air bubbles that

will affect the quality of the lacquer.

Using only the brush provided in the

Fioré Rx bottle, apply a strip of

lacquer down the middle of your nail

from cuticle to tip before following it

with lacquer on either side. Allow

lacquer to dry for at least 2 minutes.

For best results, apply a second coat

and allow to dry for 30 minutes.

Inactive ingredients

Butyl acetate, ethyl acetate, nitrocellulose, adipic acid/neopentyl glycol/trimellitic copolymer, acetyl tributyl citrate, isopropyl alcohol, propolis wax

May contain:

Stearalkonium Bentonite, Acrylates Copolymer, CI 77891, Styrene Acrylates Copolymer, CI 15850, Silica, Benzophenone-1, Trimethylpantanediyl Dibenzoate, Mica, Tin Oxide, CI 77510, CI 19140, CI 77491